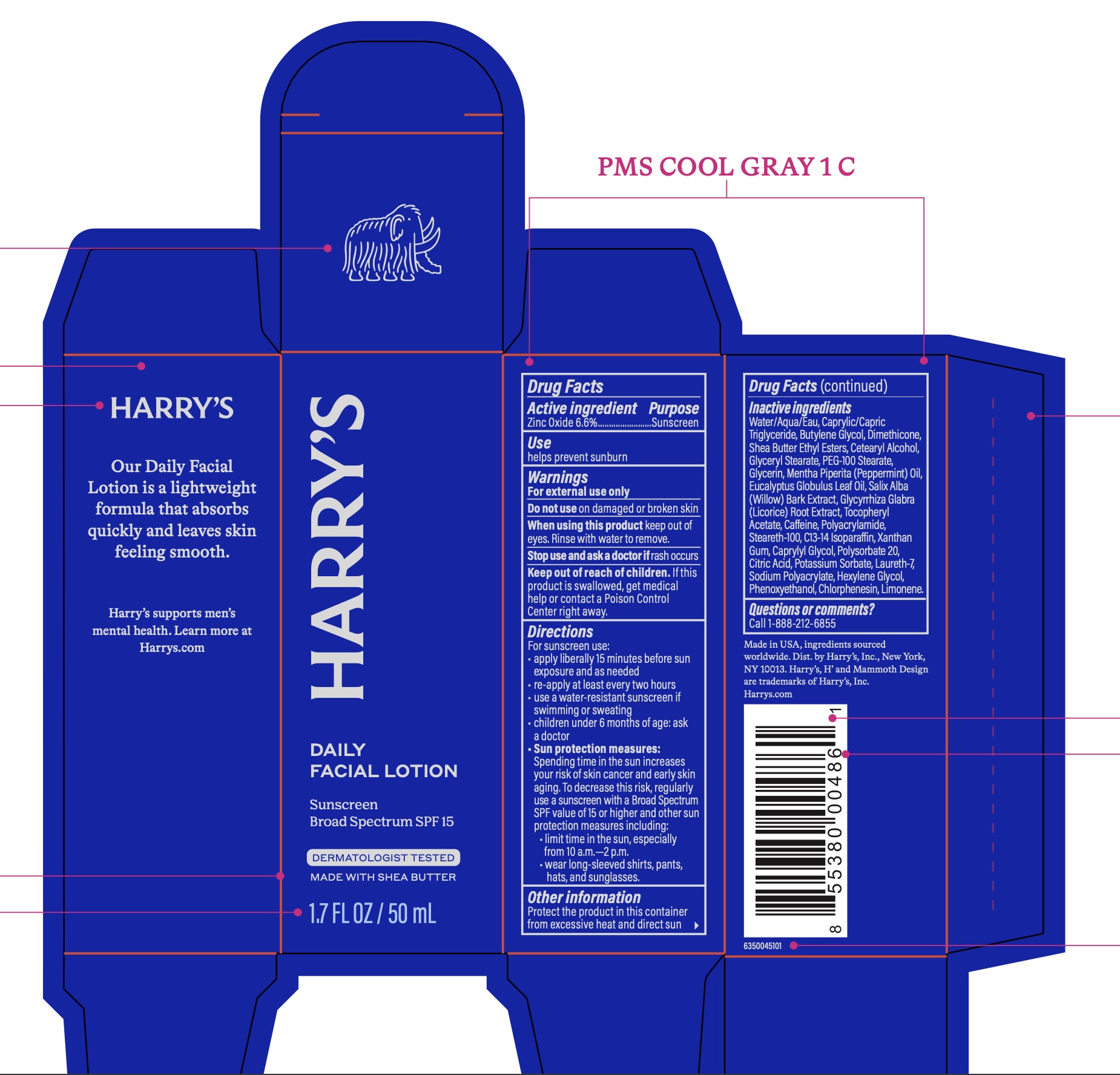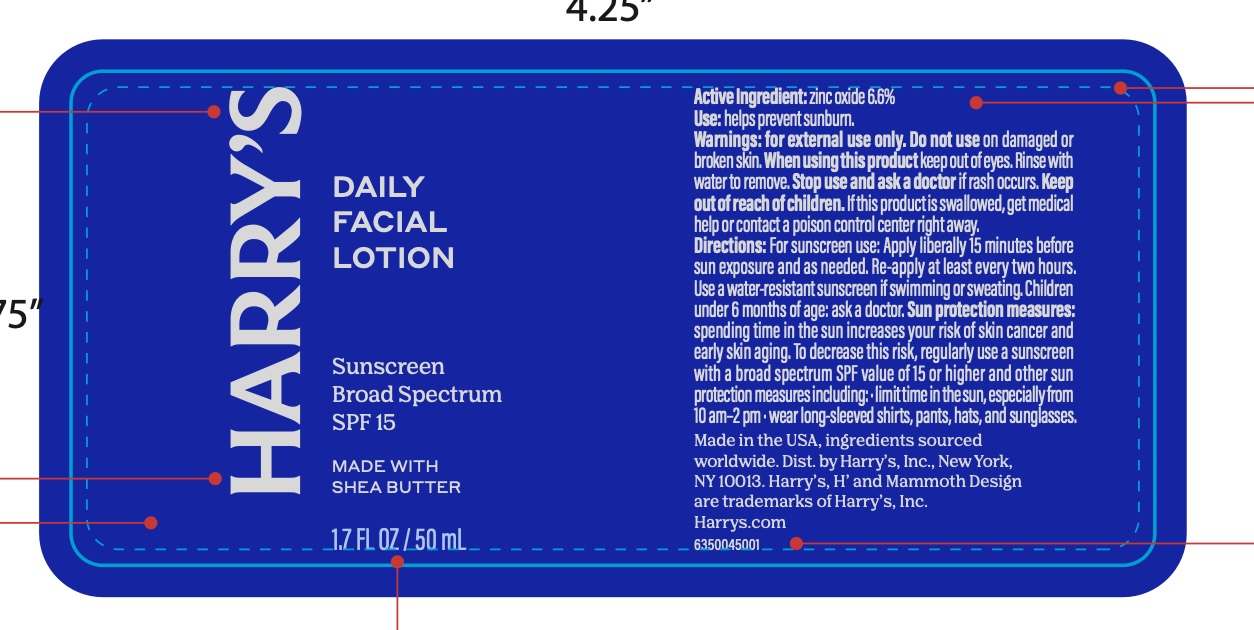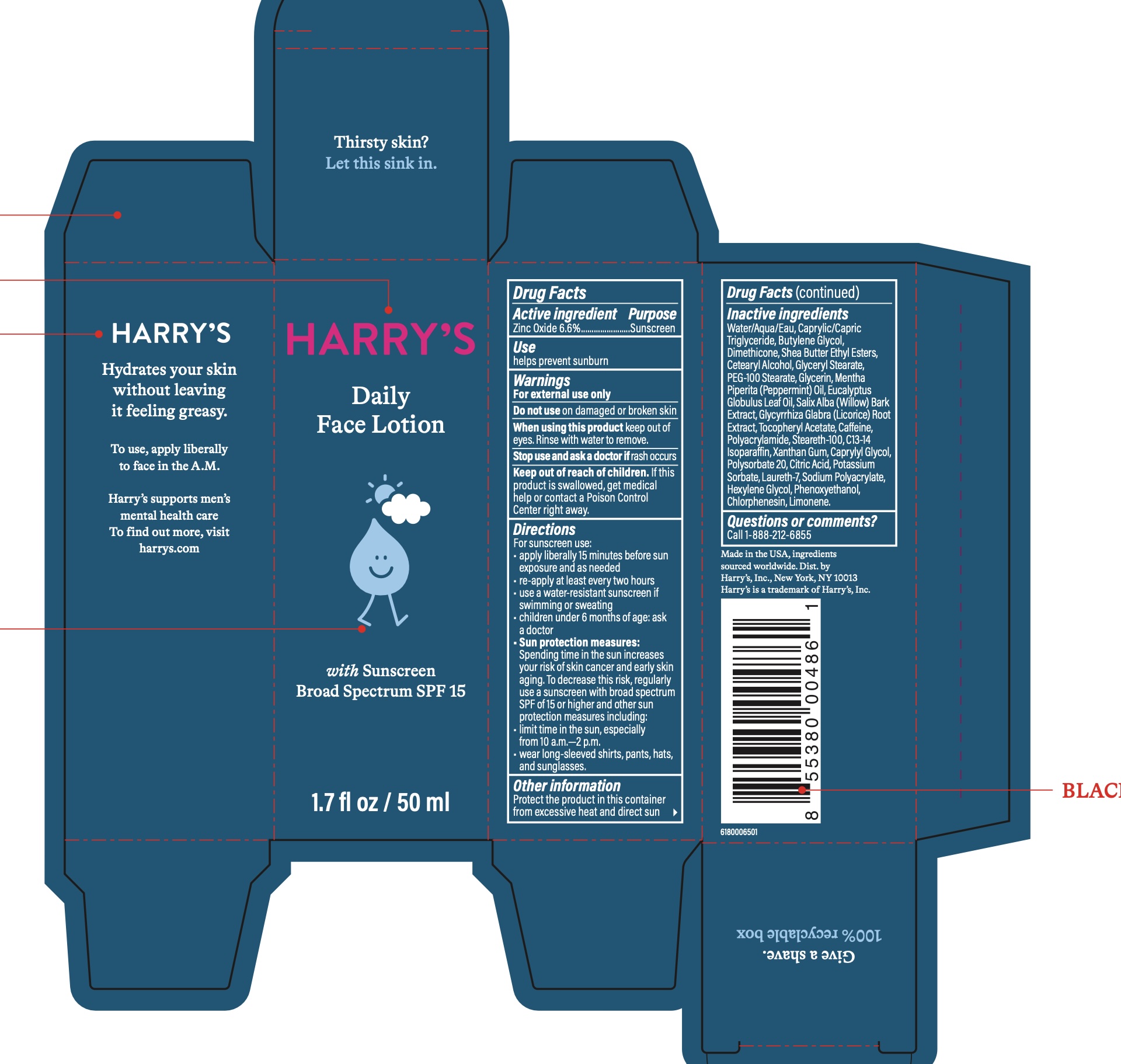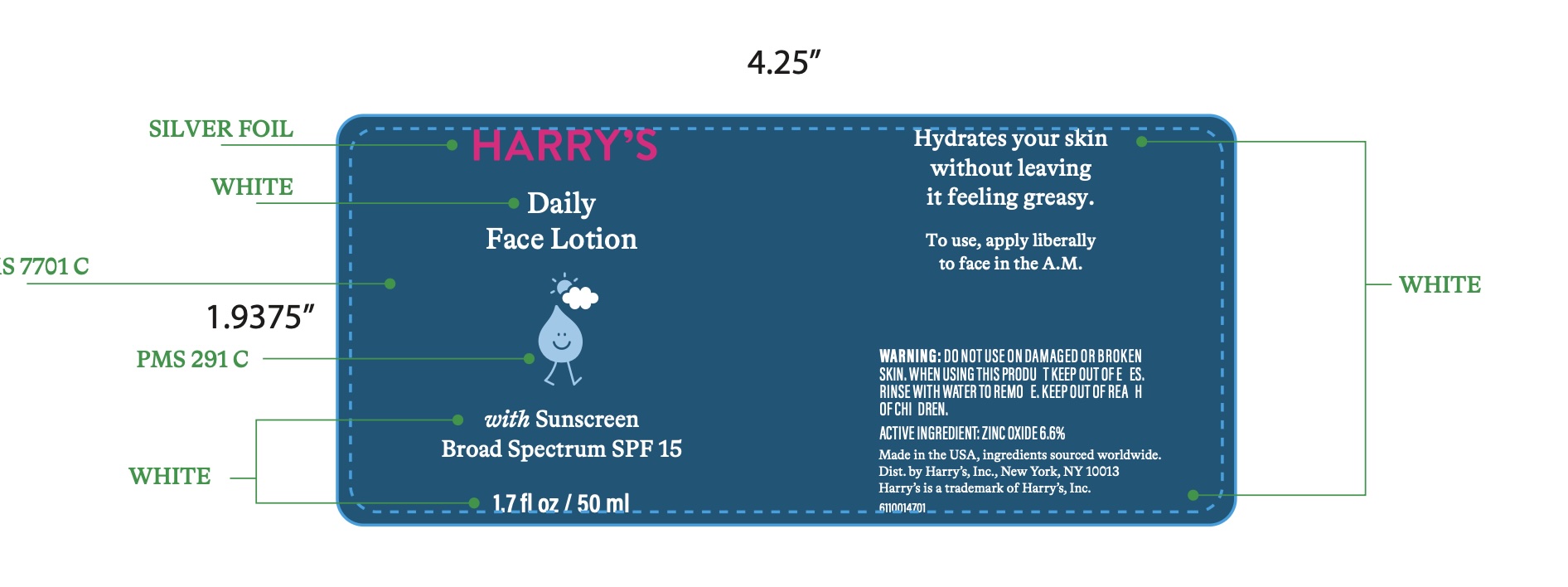 DRUG LABEL: Harrys Daily Facial SPF Broad Spectrum
NDC: 70533-016 | Form: LOTION
Manufacturer: Harry's, Inc.
Category: otc | Type: HUMAN OTC DRUG LABEL
Date: 20251208

ACTIVE INGREDIENTS: ZINC OXIDE 66 mg/1 mL
INACTIVE INGREDIENTS: PHENOXYETHANOL; CITRIC ACID; POLYSORBATE 20; POTASSIUM SORBATE; CHLORPHENESIN; MENTHA PIPERITA (PEPPERMINT) OIL; ALPHA-TOCOPHEROL ACETATE; CAFFEINE; LAURETH-7; SODIUM POLYACRYLATE (2500000 MW); GLYCERYL STEARATE; CAPRYLIC/CAPRIC TRIGLYCERIDE; GLYCYRRHIZA GLABRA (LICORICE) ROOT; WATER; EUCALYPTUS GLOBULUS LEAF OIL; LIMONENE, (+)-; GLYCERIN; SALIX ALBA BARK; CETEARYL ALCOHOL; CAPRYLYL GLYCOL; DIMETHICONE; PEG-100 STEARATE; BUTYLENE GLYCOL; SHEA BUTTER ETHYL ESTERS; XANTHAN GUM; HEXYLENE GLYCOL; POLYACRYLAMIDE (10000 MW); STEARETH-100; C13-14 ISOPARAFFIN

Harry's Daily Face Lotion SPF 15

Active Ingredient

Zinc Oxide 6.6%

Purpose

Sunscreen

Use

Helps prevent sunburn

Warnings

For external use only

Do not use on damaged or broken skin

When using this product keep out of eyes. Rinse with water to remove.

Stop use and ask a doctor if rash or irritation develops and lasts

Keep out of reach of children. If this product is swallowed, get medical help or contact a Poison Control Center right away.

Directions

For sunscreen use:

• apply liberally 15 minutes before sun exposure and as needed

• re-apply at least every two hours

• use a water-resistant sunscreen if swimming or sweating

• children under 6 months: ask a doctor

• Sun protection measures: Spending time in the sun increases your risk of skin cancer and early skin

aging. To decrease this risk, regularly use a sunscreen with broad spectrum SPF of 15 or higher and

other sun protection measures including:

• limit time in the sun, especially from 10 a.m.

• wear long-sleeve shirts, pants, hats, and sunglasses.

Other Information

Protect the product in this container from excessive heat and direct sun

Inactive Ingredients

Water/Aqua/Eau, Caprylic/Capric Triglyceride, Butylene Glycol, Dimethicone,Shea Butter Ethyl Esters, Cetearyl Alcohol, Glyceryl Stearate, PEG-100 Stearate, Glycerin, Mentha Piperita (Peppermint) Oil, Eucalyptus Globulus Leaf Oil, Salix Alba (Willow) Bark Extract, Glycyrrhiza Glabra (Licorice) Root Extract, Tocopheryl Acetate, Caffeine, Polyacrylamide, Steareth-100, C13-14 Isoparaffin, Xanthan Gum, Caprylyl Glycol, Polysorbate 20, Citric Acid, Potassium Sorbate, Laureth-7, Sodium Polyacrylate, Hexylene Glycol,

Phenoxyethanol, Chlorphenesin, Limonene.